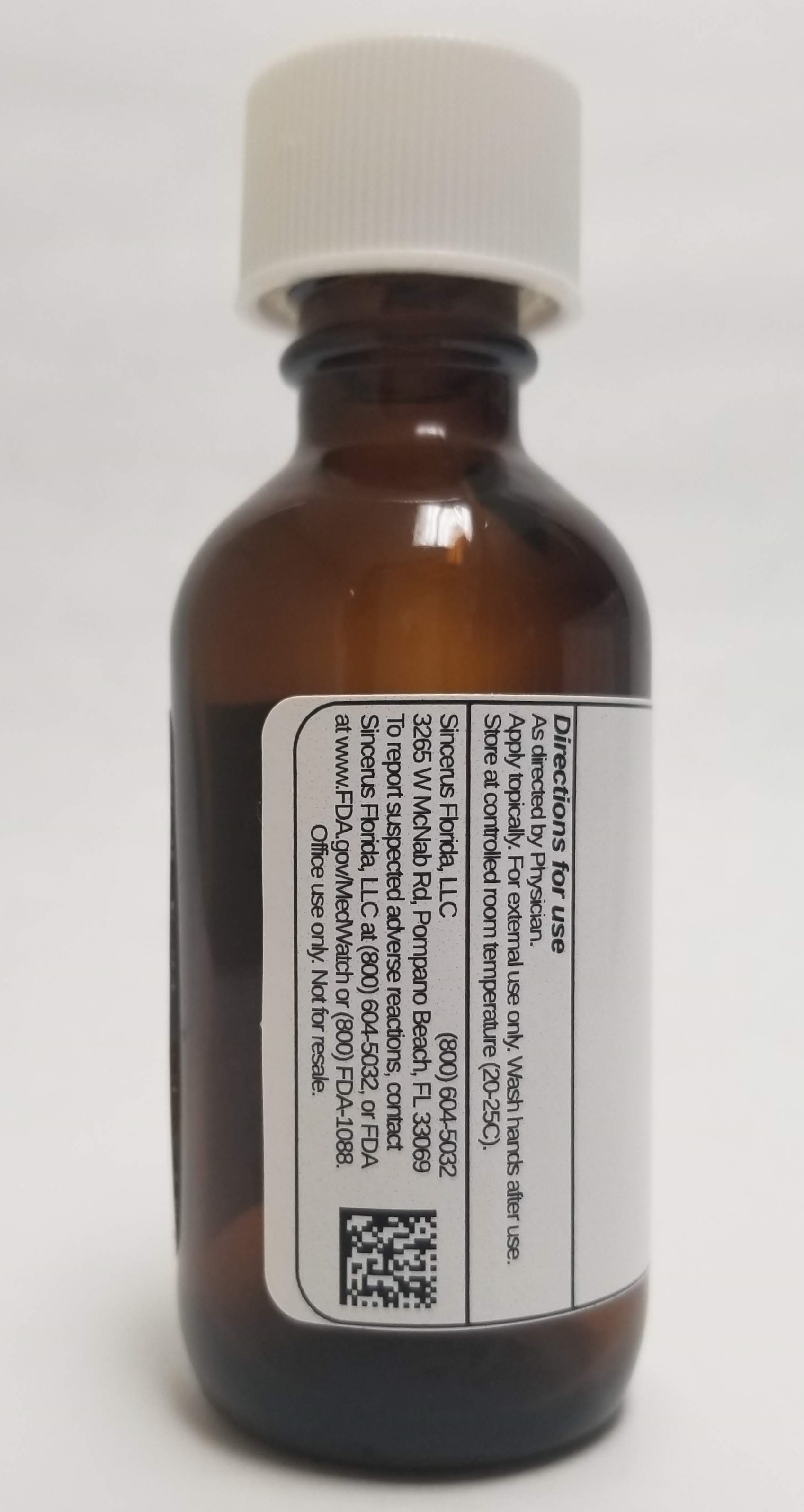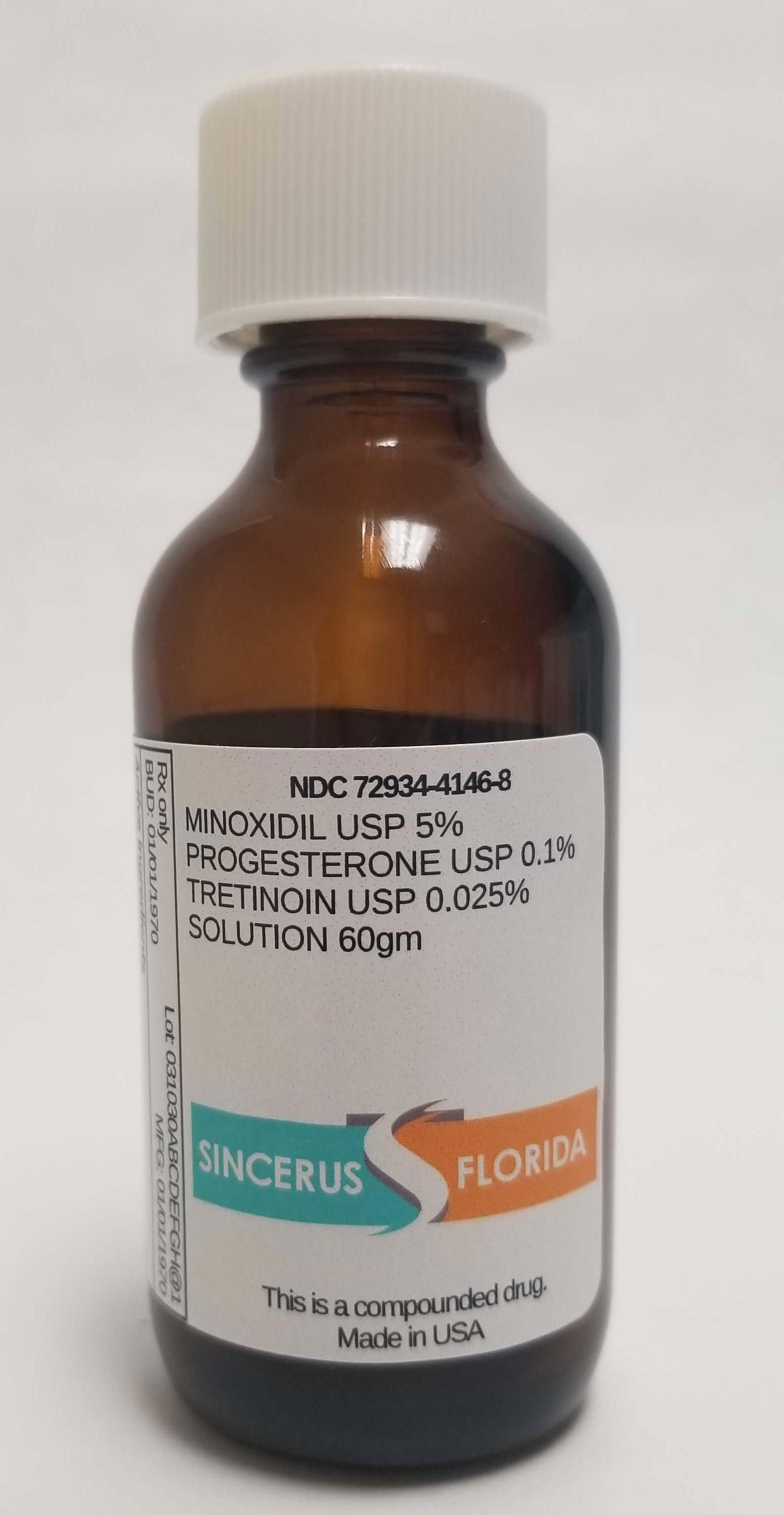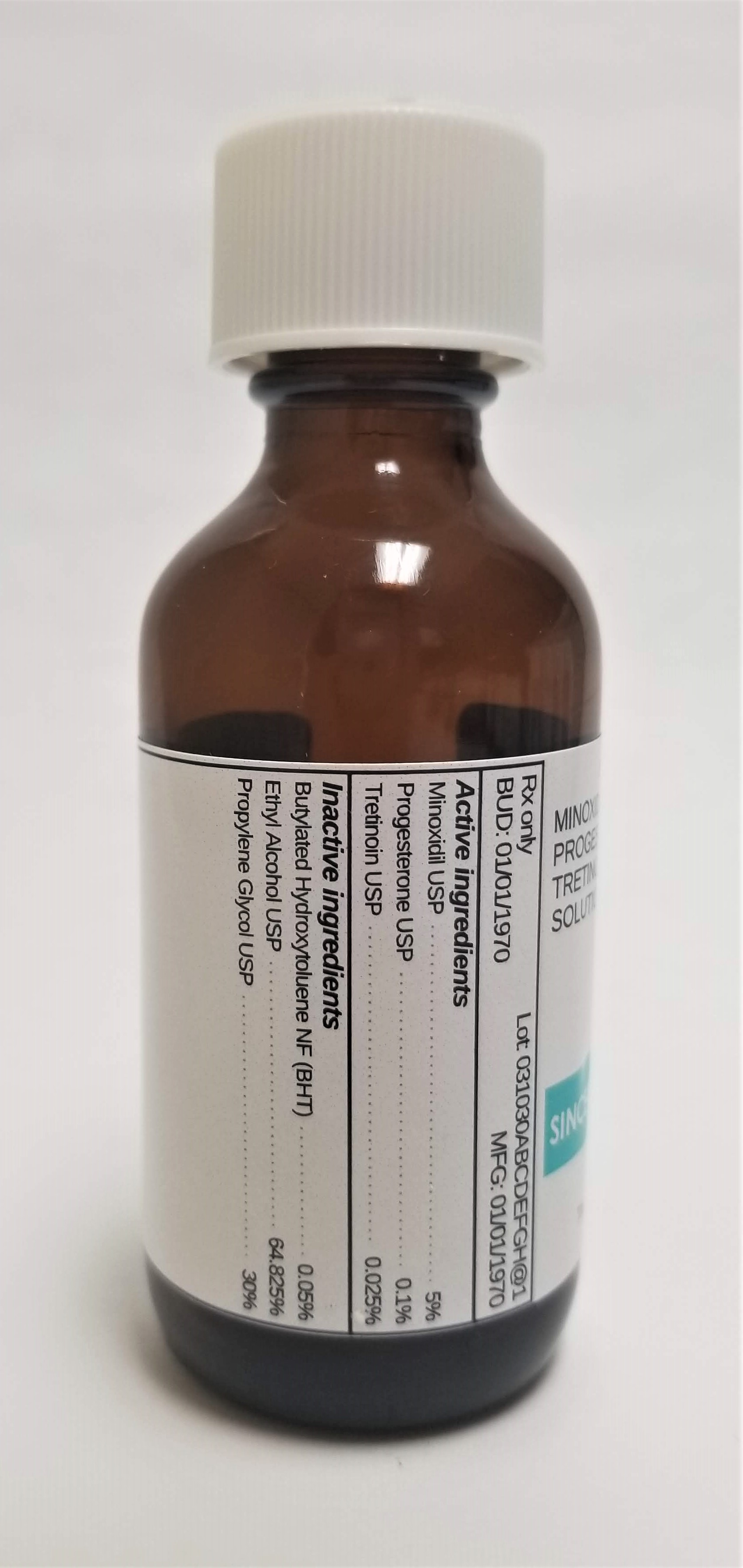 DRUG LABEL: MINOXIDIL 5% / PROGESTERONE 0.1% / TRETINOIN 0.025%
NDC: 72934-4146 | Form: SOLUTION
Manufacturer: Sincerus Florida, LLC
Category: prescription | Type: HUMAN PRESCRIPTION DRUG LABEL
Date: 20190506

ACTIVE INGREDIENTS: MINOXIDIL 5 g/100 g; PROGESTERONE 0.1 g/100 g; TRETINOIN 0.025 g/100 g

MINOXIDIL 5% / PROGESTERONE 0.1% / TRETINOIN 0.025%